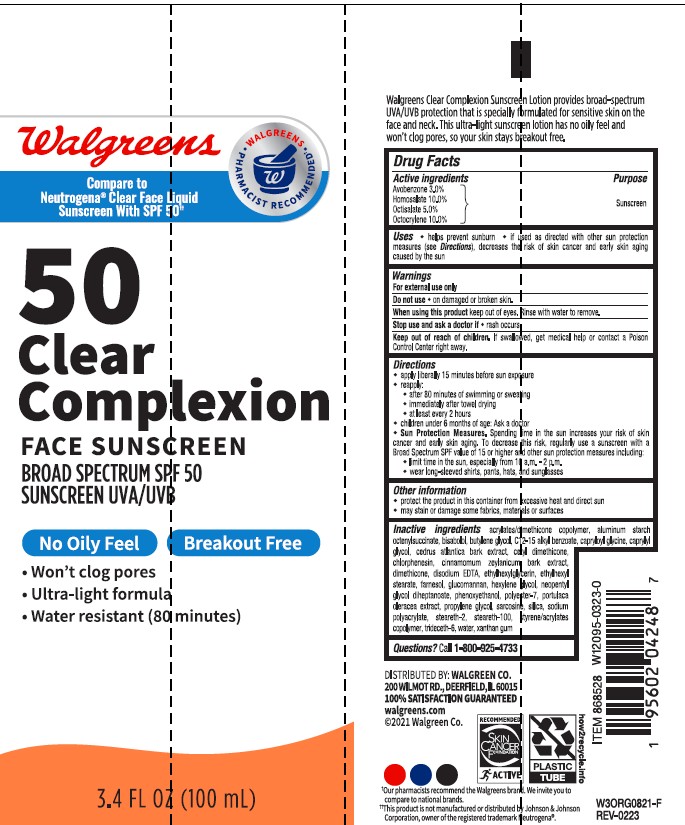 DRUG LABEL: Walgreens SPF 50 Clear Complexion Face Sunscreen
NDC: 0363-0433 | Form: LOTION
Manufacturer: WALGREEN COMPANY
Category: otc | Type: HUMAN OTC DRUG LABEL
Date: 20250324

ACTIVE INGREDIENTS: AVOBENZONE 30 mg/1 mL; HOMOSALATE 100 mg/1 mL; OCTISALATE 50 mg/1 mL; OCTOCRYLENE 100 mg/1 mL
INACTIVE INGREDIENTS: DIMETHICONE; TRIDECETH-6; ALKYL (C12-15) BENZOATE; CAPRYLYL GLYCOL; KONJAC MANNAN; PURSLANE; CHLORPHENESIN; BUTYL METHACRYLATE/METHYL METHACRYLATE/METHACRYLIC ACID/STYRENE CROSSPOLYMER; SILICON DIOXIDE; NEOPENTYL GLYCOL DIHEPTANOATE; PROPYLENE GLYCOL; EDETATE DISODIUM; CETYL DIMETHICONE 45; PHENOXYETHANOL; STEARETH-2; WATER; STEARETH-100; XANTHAN GUM; POLYESTER-7; SODIUM POLYACRYLATE (8000 MW); ETHYLHEXYLGLYCERIN; ETHYLHEXYL STEARATE; .ALPHA.-BISABOLOL, (+/-)-; BUTYLENE GLYCOL; CAPRYLOYL GLYCINE; CEDRUS ATLANTICA BARK; SARCOSINE; CINNAMON BARK OIL; FARNESOL; HEXYLENE GLYCOL; ALUMINUM STARCH OCTENYLSUCCINATE

Walgreens SPF 50 Clear Complexion Face Sunscreen

Active ingredients

Avobenzone 3.0%

Homosalate 10.0%

Octisalate 5.0%

Octocrylene 10.0%

Purpose

Sunscreen

Uses

- helps prevent sunburn
- if used as directed with other sun protection measures (see Directions), decreases the risk of skin cancer and early skin aging caused by the sun

Warnings

For external use only

Do not use

- on damaged or broken skin

When using this product

- keep out of eyes. Rinse with water to remove.

Stop use and ask doctor if

- rash occurs.

Keep out of reach of children.

If swallowed, get medical help or contact a Poison Control Center right away.

Directions

- apply liberally 15 minutes before sun exposure

- reapply:
- after 80 minutes of swimming or sweating
- immediately after towel drying
- at least every 2 hours

- children under 6 months of age: Ask a doctor

- Sun Protection Measures. Spending time in the sun increases your risk of skin cancer and early skin aging. To decrease this risk, regularly use a sunscreen with a Broad Spectrum SPF value of 15 or higher and other sun protection measures including:
- limit time in the sun, especially from 10 a.m. - 2 p.m.
- wear long-sleeved shirts, pants, hats, and sunglasses

Other information

• protect the product in this container from excessive heat and direct sun
• may stain or damage some fabrics, materials or surfaces

Inactive ingredients

acrylates/dimethicone copolymer, aluminum starch octenylsuccinate, bisabolol, butylene glycol, C12-15 alkyl benzoate, capryloyl glycine, caprylyl glycol, cedrus atlantica bark extract, cetyl dimethicone, chlorphenesin, cinnamomum zeylanicum bark extract, dimethicone, disodium EDTA, ethylhexylglycerin, ethylhexyl stearate, farnesol, glucomannan, hexylene glycol, neopentyl glycol diheptanoate, phenoxyethanol, polyester-7, portulaca oleracea extract, propylene glycol, sarcosine, silica, sodium polyacrylate, steareth-2, steareth-100, styrene/acrylates copolymer, trideceth-6, water, xanthan gum